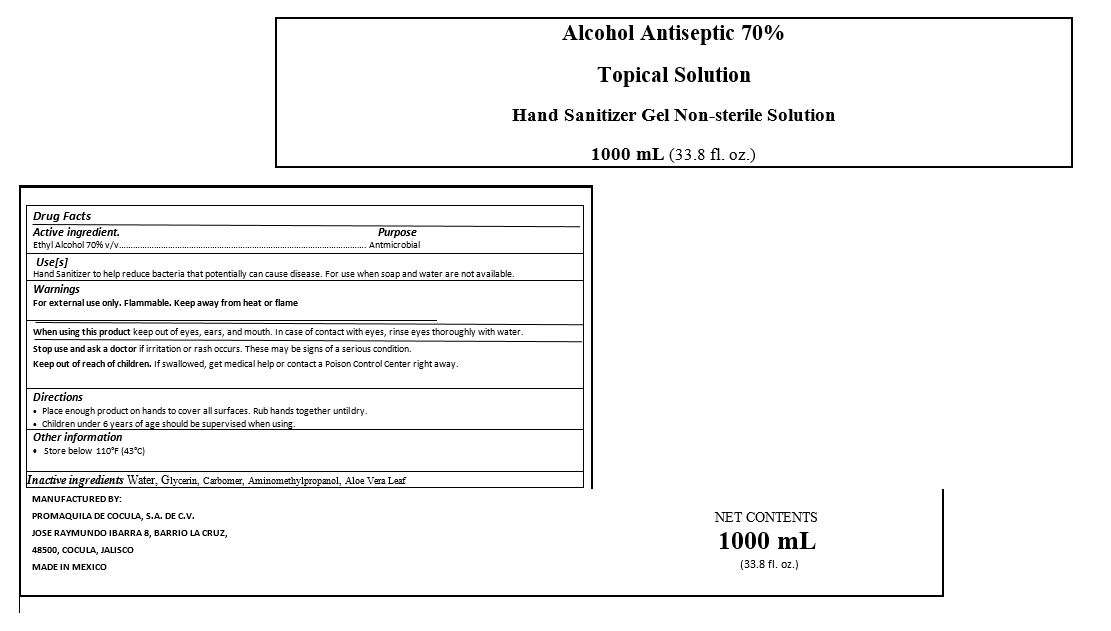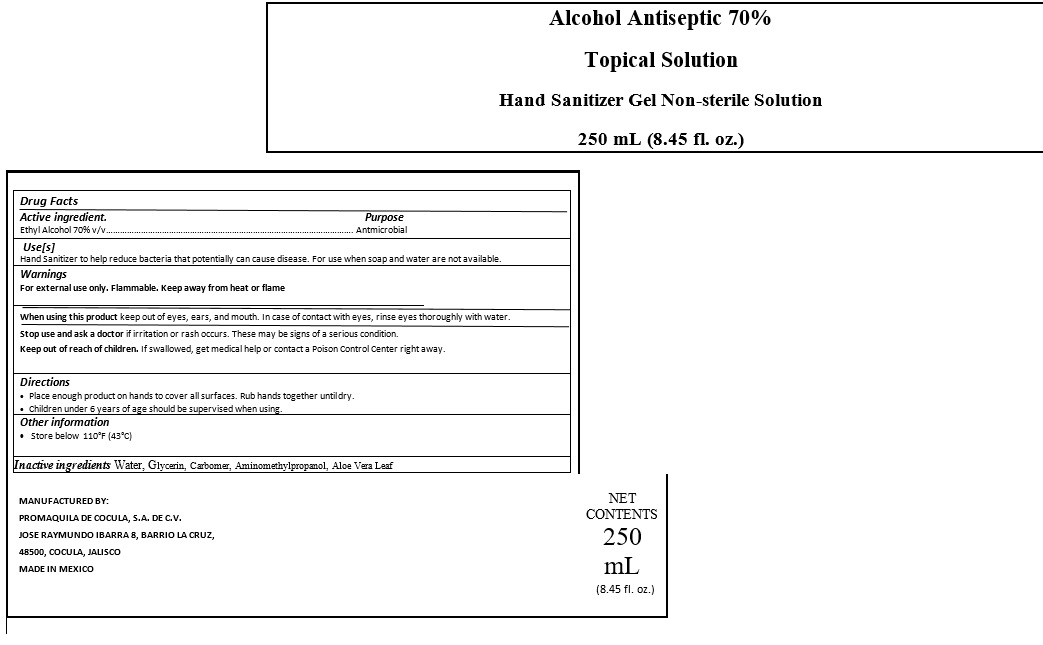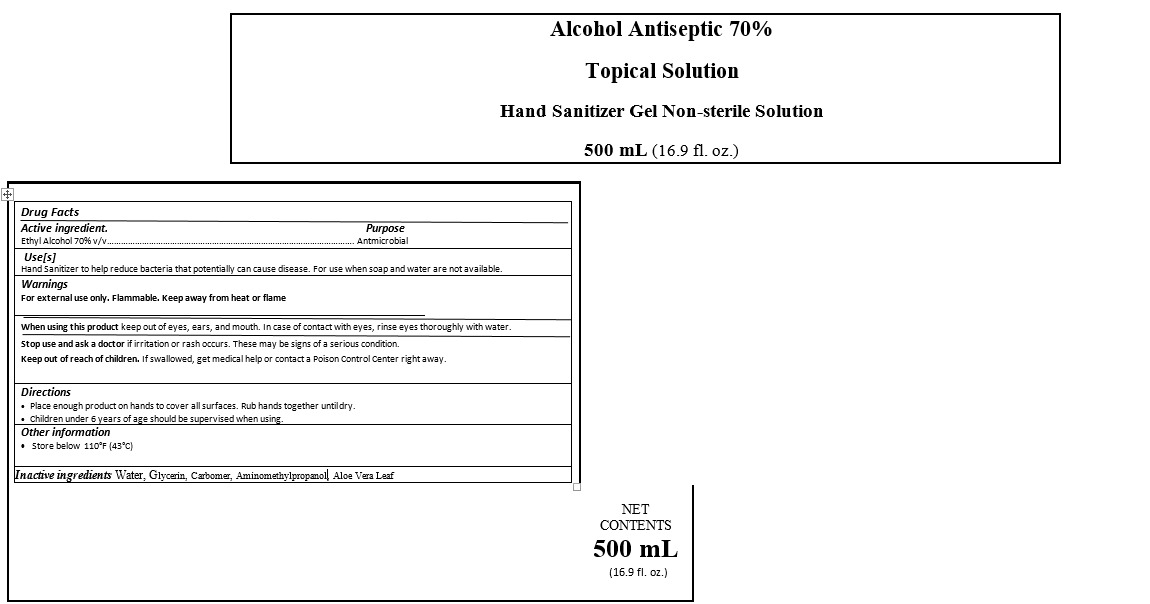 DRUG LABEL: IBARRA
NDC: 79577-0002 | Form: GEL
Manufacturer: PROMAQUILA DE COCULA, S.A. DE C.V.
Category: otc | Type: HUMAN OTC DRUG LABEL
Date: 20200804

ACTIVE INGREDIENTS: ALCOHOL 0.7 mL/1 mL
INACTIVE INGREDIENTS: GLYCERIN 0.00302 mL/1 mL; WATER 0.28711 mL/1 mL; CARBOMER 940 0.0043 mL/1 mL; AMINOMETHYLPROPANOL 0.00279 mL/1 mL; ALOE VERA LEAF 0.00278 mL/1 mL

HAND SANITIZER GEL IBARRA

ACTIVE INGREDIENTS

Active ingredient Ethyl Alcohol 70% v/v

PURPOSE

Purpose Antmicrobial

INDICATIONS AND USAGE

Use[s]

Hand Sanitizer to help reduce bacteria that potentially can cause disease. For use when soap and water are not available.

DOSAGE AND ADMINISTRATION

Directions

Place enough product on hands to cover all surfaces. Rub hands together until dry.

WARNINGS AND PRECAUTIONS

Store below 110°F (43°C)

Children under 6 years of age should be supervised when using.

WARNINGS

For external use only. Flammable. Keep away from heat or flame

STOP USE SECTION

Stop use and ask a doctor if irritation or rash occurs. These may be signs of a serious condition.

Keep out of reach of children. If swallowed, get medical help or contact a Poison Control Center right away.

INACTIVE IGREDIENTS

Inactive ingredients Water (Aqua), Glycerin, Carbomer, Triethanolamine